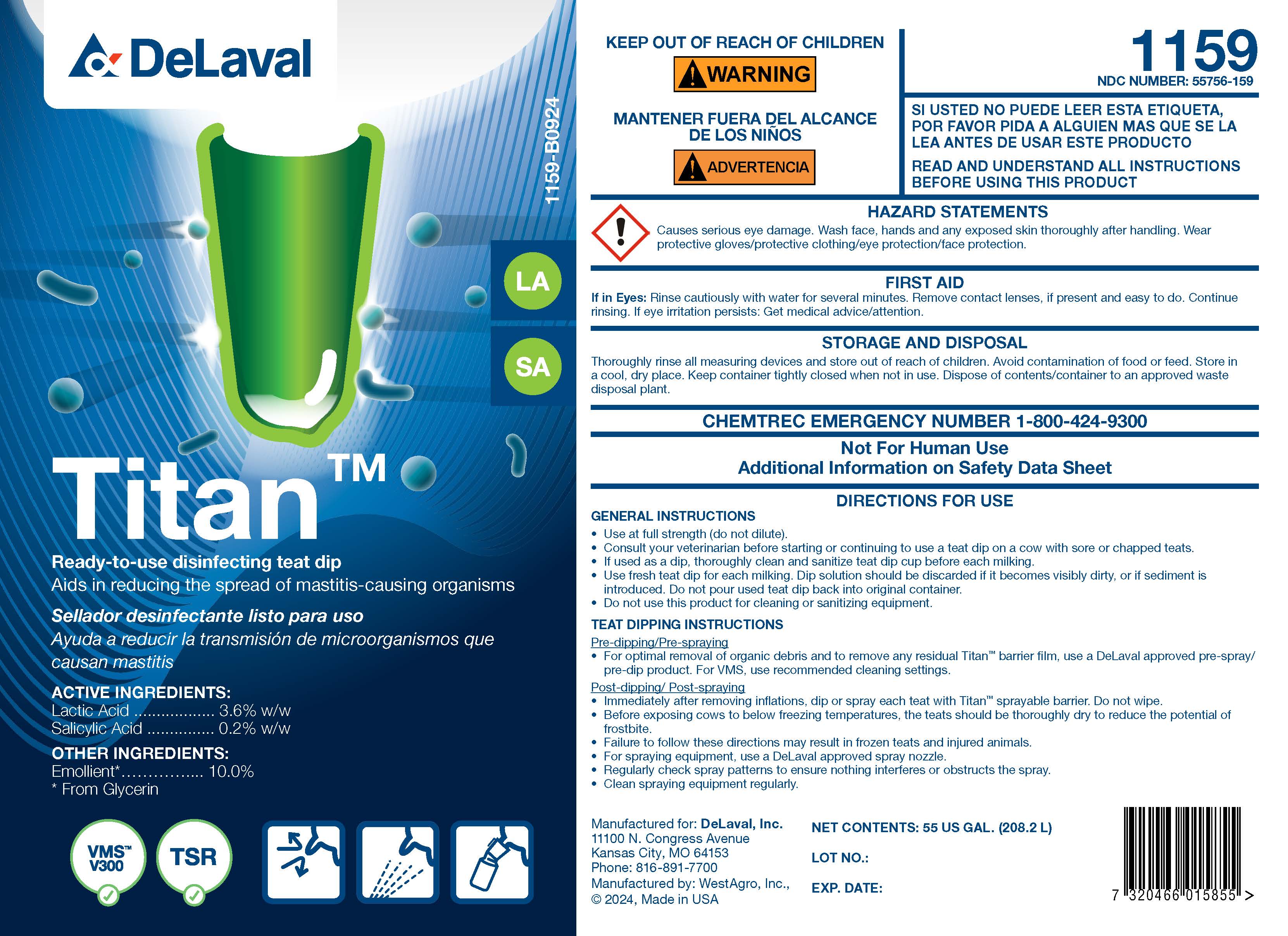 DRUG LABEL: Titan
NDC: 55756-159 | Form: SOLUTION
Manufacturer: DeLaval
Category: animal | Type: OTC ANIMAL DRUG LABEL
Date: 20250107

ACTIVE INGREDIENTS: LACTIC ACID 36 g/1 L; SALICYLIC ACID 2 g/1 L
INACTIVE INGREDIENTS: GLYCERIN; XANTHAN GUM; POVIDONE K30; C9-11 PARETH-8; SODIUM CAPRYLYL SULFONATE; SODIUM HYDROXIDE; FD&C YELLOW NO. 5; FD&C BLUE NO. 1; WATER

TitanTM

ACTIVE INGREDIENTS:

Lactic Acid ...................... 3.6% w/w

Salicylic Acid ................... 0.2% w/w

INACTIVE INGREDIENT

OTHER INGREDIENTS:

* Emollient .................. 10.0%

* From Glycerin

KEEP OUT OF REACH OF CHILDREN

! WARNING

PRECAUTIONS

READ AND UNDERSTAND ALL INSTRUCTIONS BEFORE USING THIS PRODUCT

WARNINGS

HAZARD STATEMENTS

! Causes serious eye damage. Wash face, hands and any exposed skin thoroughly after handling. Wear protective gloves/protective clothing/eye protection/face protection.

FIRST AID

If in Eyes: Rinse cautiously with water for several minutes. Remove contact lenses, if present and easy to do. Continue rinsing. If eye irritation persists; Get medical advice/attention.

STORAGE AND DISPOSAL

Thoroughly rinse all measuring devices and store out of reach of children. Avoid contamination of food or feed. Store in a cool, dry place. Keep container tightly closed when not in use. Dispose of contents/container to an approved waste disposal plant.

CHEMTREC EMERGENCY NUMBER 1-800-424-9300

PRECAUTIONS

Not For Human Use

Additional Information on Safety Data Sheet

DOSAGE AND ADMINISTRATION

DIRECTIONS FOR USE

GENERAL INSTRUCTIONS

- Use at full strength (do not dilute).
- Consult your veterinarian before starting or continuing to use a teat dip on a cow with sore or chapped teats.
- If used as a dip, thoroughly clean and sanitize teat dip cup before each milking.
- Use fresh teat dip for each milking. Dip solution should be discarded if it becomes visibly dirty, or if sediment is introduced. Do not pour used teat dip back into original container.
- Do not use this product for cleaning or sanitizing equipment.

TEAT DIPPING INSTRUCTIONS

Pre-dipping/Pre-spraying

- For optimal removal of organic debris and to remove any residual TitanTM barrier film, use a DeLaval approved pre-spray/pre-dip product. For VMS, use recommended cleaning settings.

Post-dipping/Post-spraying

- Immediately after removing inflations, dip or spray each teat with TitanTM sprayable barrier. Do not wipe.
- Before exposing cows to below freezing temperatures, the teats should be thoroughly dry to reduce the potential of frostbite.
- Failure to follow these directions may result in frozen teats and injured animals.
- For spraying equipment, use a DeLaval approved spray nozzle.
- Regularly check spray patterns to ensure nothing interferes or obstructs the spray.
- Clean spraying equpment regularly.

NET CONTENTS: US GAL (L)

LOT NO.:

EXP. DATE:

Manufactured for: DeLaval, Inc.

11100 N. Congress Avenue

Kansas City, MO 64153

Phone: 816-891-7700

Manufactured by: WestAgro, Inc.,

© 2024, Made in USA

PACKAGE LABEL

Add image transcription here...